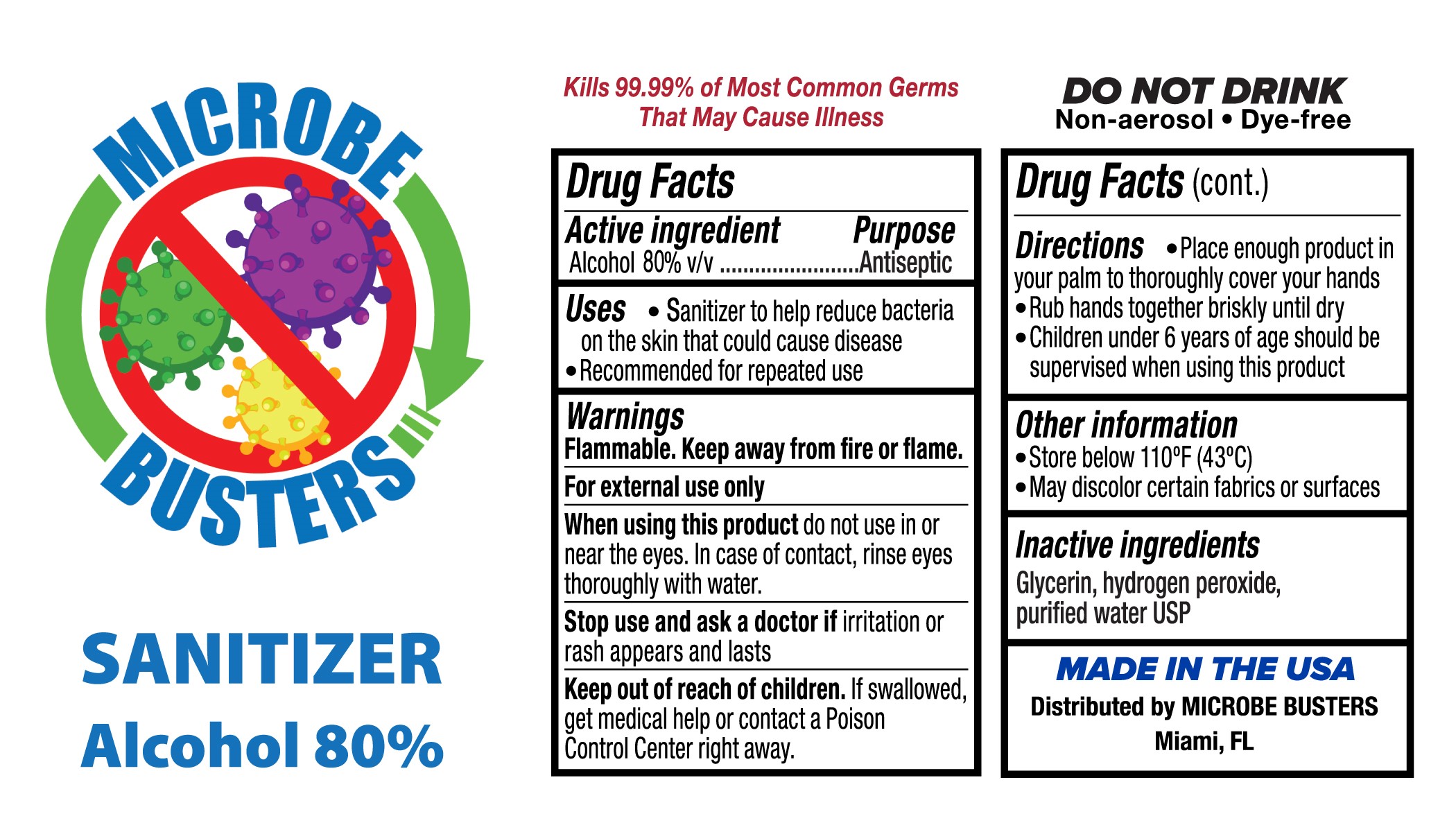 DRUG LABEL: Hand Sanitizer
NDC: 77183-5195 | Form: LIQUID
Manufacturer: Tekna Fill, Inc.
Category: otc | Type: HUMAN OTC DRUG LABEL
Date: 20200626

ACTIVE INGREDIENTS: ALCOHOL 80 mL/100 mL
INACTIVE INGREDIENTS: GLYCERIN; HYDROGEN PEROXIDE; WATER

This is a hand sanitizer manufactured according to the Temporary Policy for Preparation of Certain Alcohol-Based Hand Sanitizer Products During the Public Health Emergency (CoViD-19); Guidance for Industry.

The hand sanitizer is manufactured using only the following United States Pharmacopoeia (USP) grade ingredients in the preparation of the product (percentage in final product formulation) consistent with World Health Organization (WHO) recommendations:

1. Alcohol (ethanol) (USP or Food Chemical Codex (FCC) grade) (80%, volume/volume (v/v)) in an aqueous solution denatured according to Alcohol and Tobacco Tax and Trade Bureau regulations in 27 CFR part 20.
2. Glycerol (1.45% v/v).
3. Hydrogen peroxide (0.125% v/v).
4. Sterile distilled water or boiled cold water.

The firm does not add other active or inactive ingredients. Different or additional ingredients may impact the quality and potency of the product.

Active Ingredient(s)

Alcohol 80% v/v. Purpose: Antiseptic

Purpose

Antiseptic, Hand Sanitizer

Use

Sanitizer to help reduce bacteria on the skin that could cause disease. Recommeded for repeated use

Warnings

Flammable. Keep away from fire or flame. For external use only.

Do not use

- for children less than 2 months of age
- on open skin wounds.

When using this product do not use in or near the eyes. In case of contact, rinse eyes thoroughly with water.
Stop use and ask a doctor if irritation or rash appears and lasts.
Keep out of reach of children. If swallowed, get medical help or contact a Poison Control Center right away.

Stop use and ask a doctor if irritation or rash appears and lasts

Keep out of reach of children. If swallowed, get medical help or contact a Poison Control Center right away.

Directions

- Place enough product in your palm to thoroughly cover your hands.
- Rub hands together briskly until dry.
- Children under 6 years of age should be supervised when using this product

Other information

- Store below 110oF (43oC)
- May discolor certain fabrics or surfaces

Inactive ingredients

Glycerin, hydrogen peroxide, purified water USP

Warnings:

Flammable. Keep away from fire or flame.

For external use only

When using this product do not use in or near the eyes. In case of contact, rinse eyes thoroughly with water.

Stop use and ask a doctor if irritation or rash appears and lasts

Keep out of reach of children. If swallowed, get medical help or contact a Poison Control Center right away.

Uses:

- Sanitizer to help reduce bacteria on the skin that could cause diease
- Recommended for repeated use

Directions:

- Place enough product in your palm to thoroughly cover your hands
- Rub hands together briskly unitl dry
- Children under 6 years of age should be supervised when using this product

Package Label - Principal Display Panel

18900 mL NDC: 77183-5195-0

18900mL in ONE PAIL